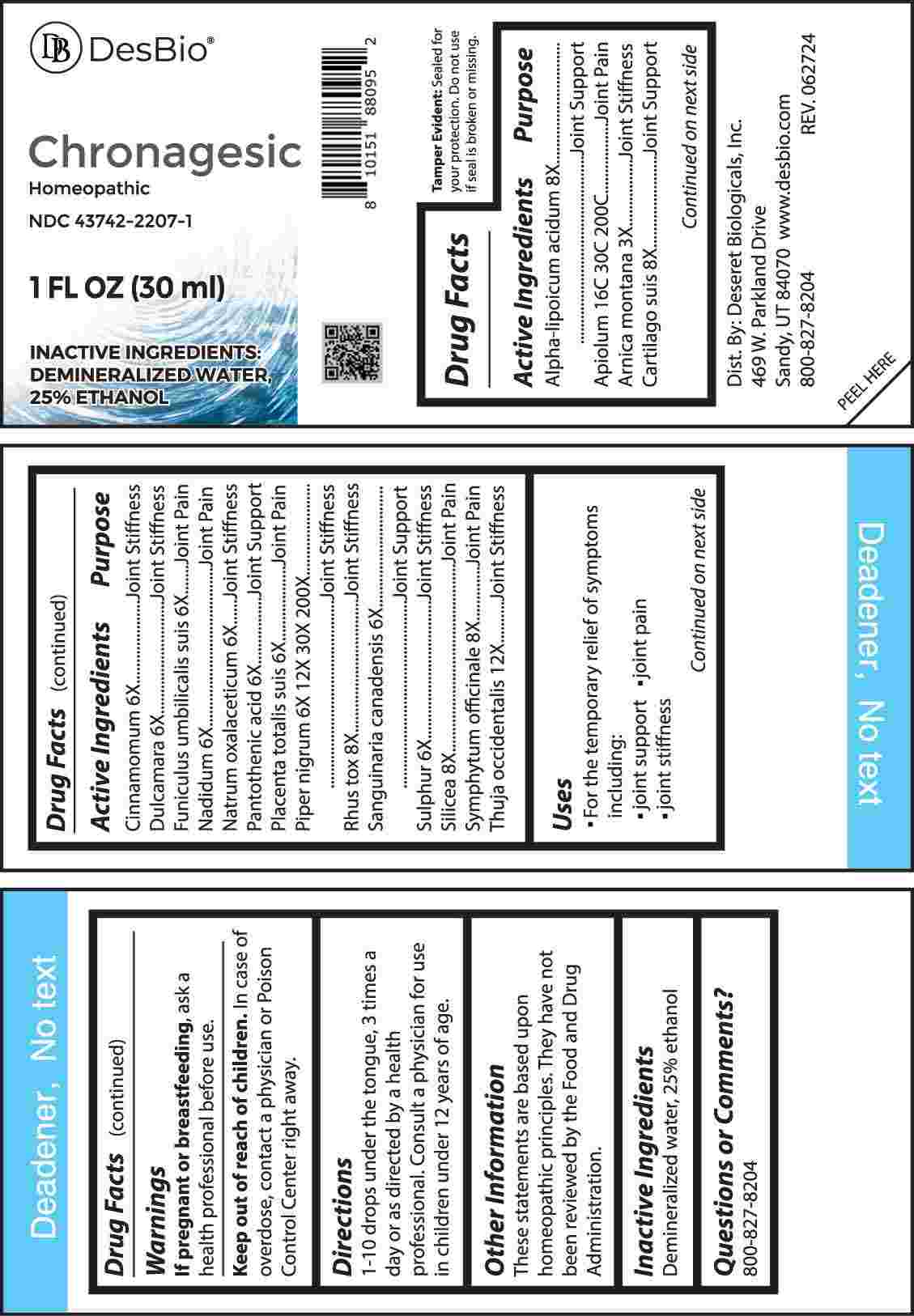 DRUG LABEL: Chronagesic
NDC: 43742-2207 | Form: LIQUID
Manufacturer: Deseret Biologicals, Inc.
Category: homeopathic | Type: HUMAN OTC DRUG LABEL
Date: 20241108

ACTIVE INGREDIENTS: ALPHA LIPOIC ACID 8 [hp_X]/1 mL; APIOLE (PARSLEY) 16 [hp_C]/1 mL; ARNICA MONTANA WHOLE 3 [hp_X]/1 mL; SUS SCROFA CARTILAGE 8 [hp_X]/1 mL; CINNAMON 6 [hp_X]/1 mL; SOLANUM DULCAMARA TOP 6 [hp_X]/1 mL; SUS SCROFA UMBILICAL CORD 6 [hp_X]/1 mL; NADIDE 6 [hp_X]/1 mL; SODIUM DIETHYL OXALACETATE 6 [hp_X]/1 mL; PANTOTHENIC ACID 6 [hp_X]/1 mL; SUS SCROFA PLACENTA 6 [hp_X]/1 mL; GREEN PEPPERCORN 6 [hp_X]/1 mL; TOXICODENDRON PUBESCENS LEAF 8 [hp_X]/1 mL; SANGUINARIA CANADENSIS ROOT 6 [hp_X]/1 mL; SULFUR 6 [hp_X]/1 mL; SILICON DIOXIDE 8 [hp_X]/1 mL; COMFREY ROOT 8 [hp_X]/1 mL; THUJA OCCIDENTALIS LEAFY TWIG 12 [hp_X]/1 mL
INACTIVE INGREDIENTS: WATER; ALCOHOL

DRUG FACTS:

ACTIVE INGREDIENTS:

Alpha-Lipoicum Acidum 8X, Apiolum 16C, 30C, 200C, Arnica Montana 3X, Cartilago Suis 8X, Cinnamomum 6X, Dulcamara 6X, Funiculus Umbilicalis Suis 6X, Nadidum 6X, Natrum Oxalaceticum 6X, Pantothenic Acid 6X, Placenta Totalis Suis 6X, Piper Nigrum 6X, 12X, 30X, 200X, Rhus Tox 8X, Sanguinaria Canadensis 6X, Sulphur 6X, Silicea 8X, Symphytum Officinale 8X, Thuja Occidentalis 12X.

PURPOSE:

Alpha-Lipoicum Acidum – Joint Support, Apiolum – Joint Pain, Arnica Montana – Joint Stiffness, Cartilago Suis – Joint Support, Cinnamomum – Joint Stiffness, Dulcamara – Joint Stiffness, Funiculus Umbilicalis Suis – Joint Pain, Nadidum – Joint Pain, Natrum Oxalaceticum – Joint Stiffness, Pantothenic Acid – Joint Support, Placenta Totalis Suis – Joint Pain, Piper Nigrum – Joint Stiffness, Rhus Tox – Joint Stiffness, Sanguinaria Canadensis – Joint Support, Sulphur – Joint Stiffness, Silicea – Joint Pain, Symphytum Officinale – Joint Pain, Thuja Occidentalis – Joint Stiffness

USES:

• For the temporary relief of symptoms including:

• joint support • joint pain • joint stiffness

These statements are based upon homeopathic principles. They have not been reviewed by the Food and Drug Administration.

WARNINGS:

If pregnant or breast-feeding, ask a health professional before use.

Keep out of reach of children. In case of overdose, contact a physician or Poison Control Center right away.

Tamper Evident: Sealed for your protection. Do not use if seal is broken or missing.

KEEP OUT OF REACH OF CHILDREN:

In case of overdose, contact a physician or Poison Control Center right away.

DIRECTIONS:

1-10 drops under the tongue, 3 times a day or as directed by a health professional. Consult a physician for use in children under 12 years of age.

INACTIVE INGREDIENTS:

Demineralized water, 25% ethanol

QUESTIONS:

Dist. by: Deseret Biologicals, Inc.

469 W. Parkland Drive

Sandy, UT 84070

www.desbio.com

800-827-8204

PACKAGE LABEL DISPLAY:

DesBio

Chronagesic

Homeopathic

NDC 43742-2207-1

1 FL OZ (30 ml)